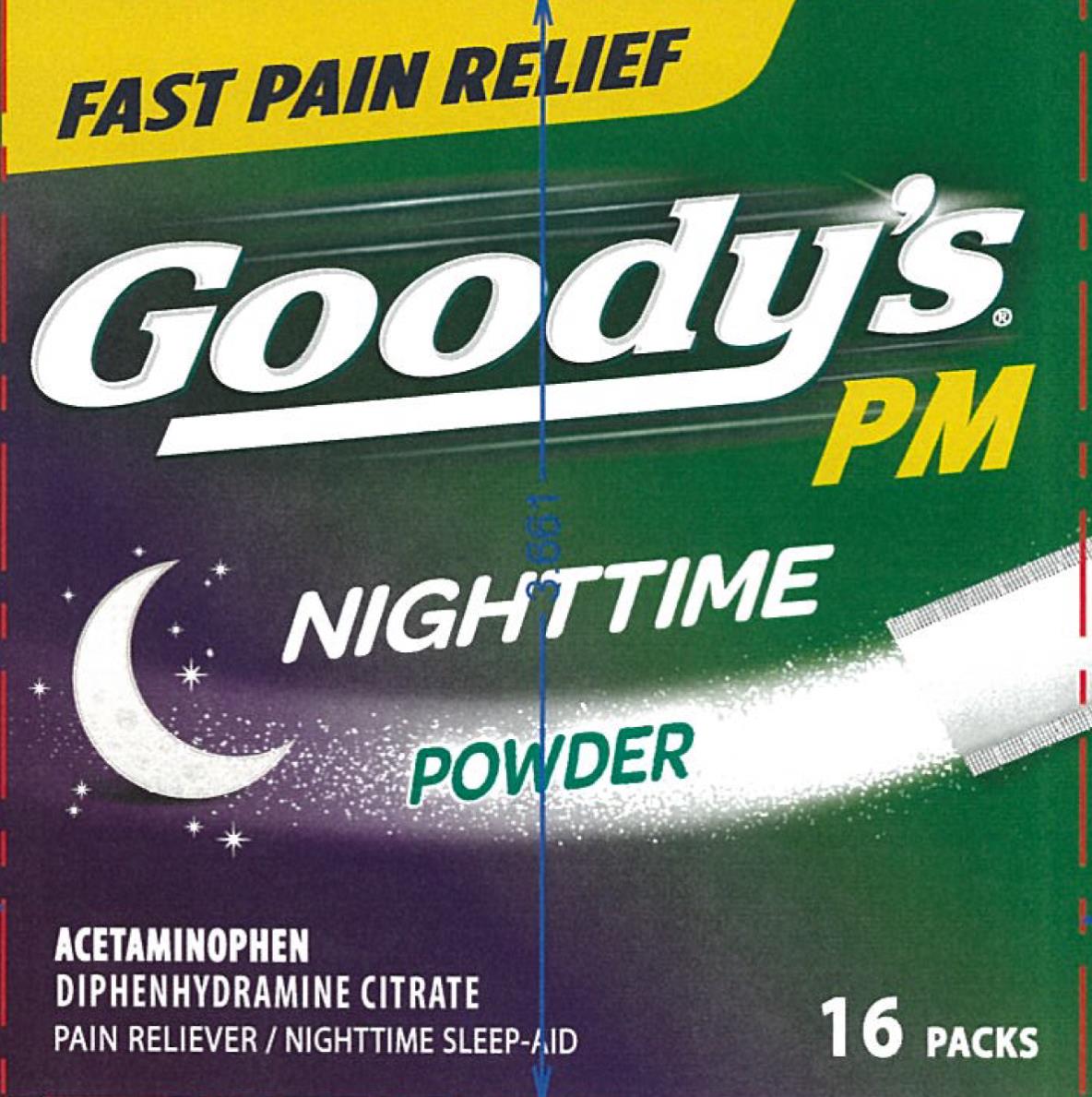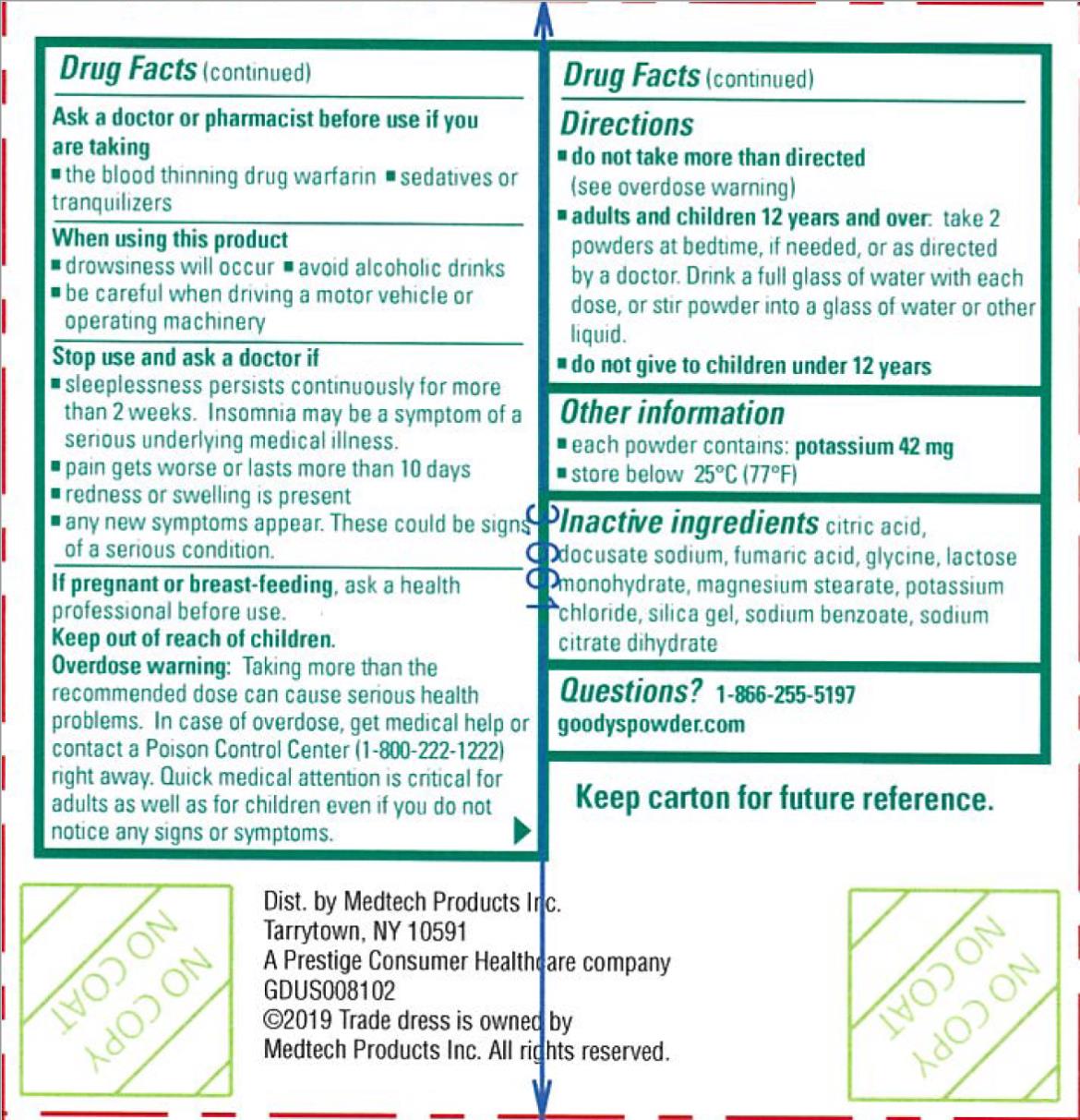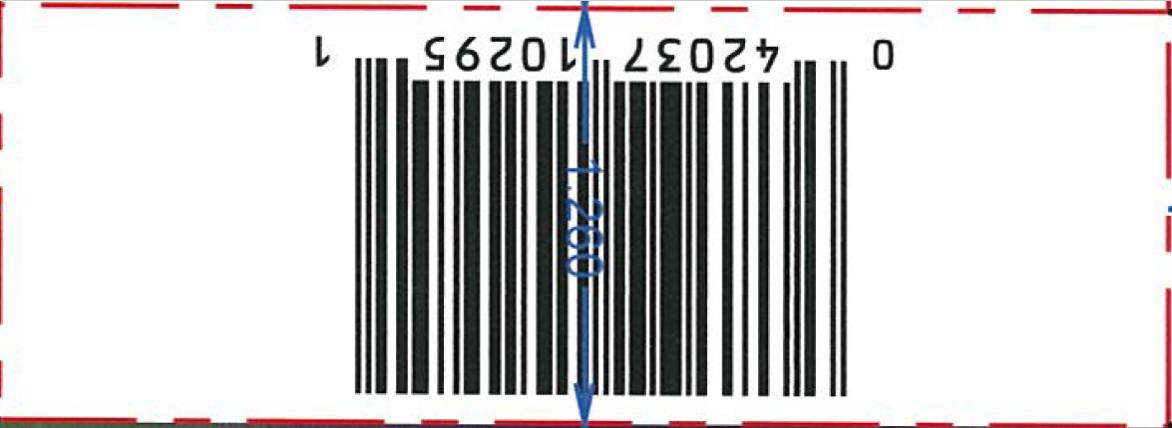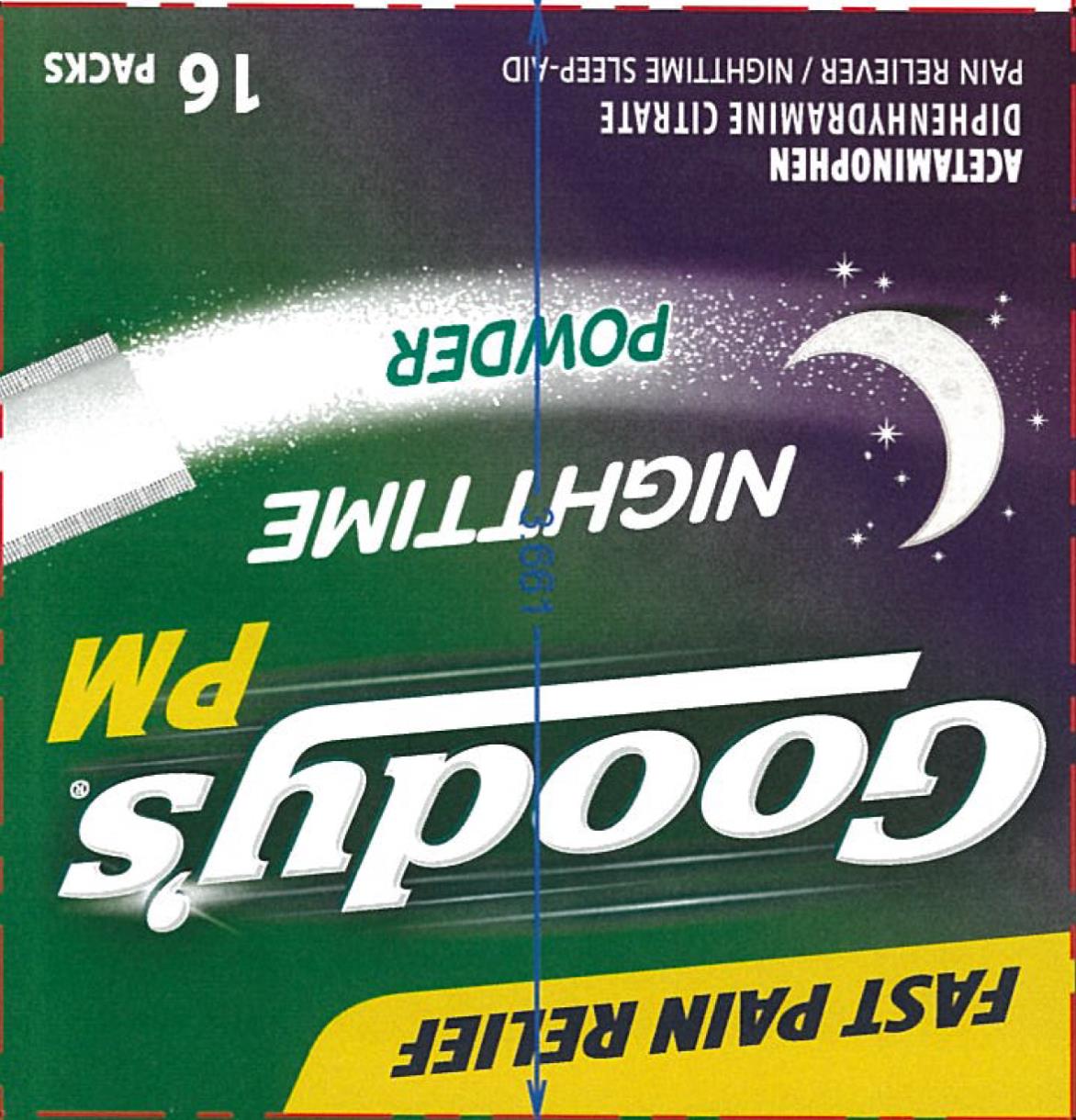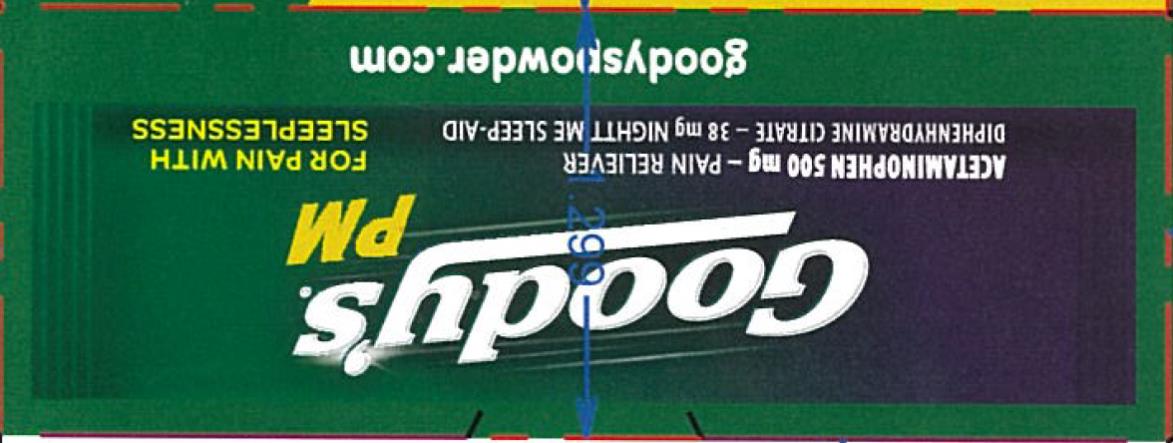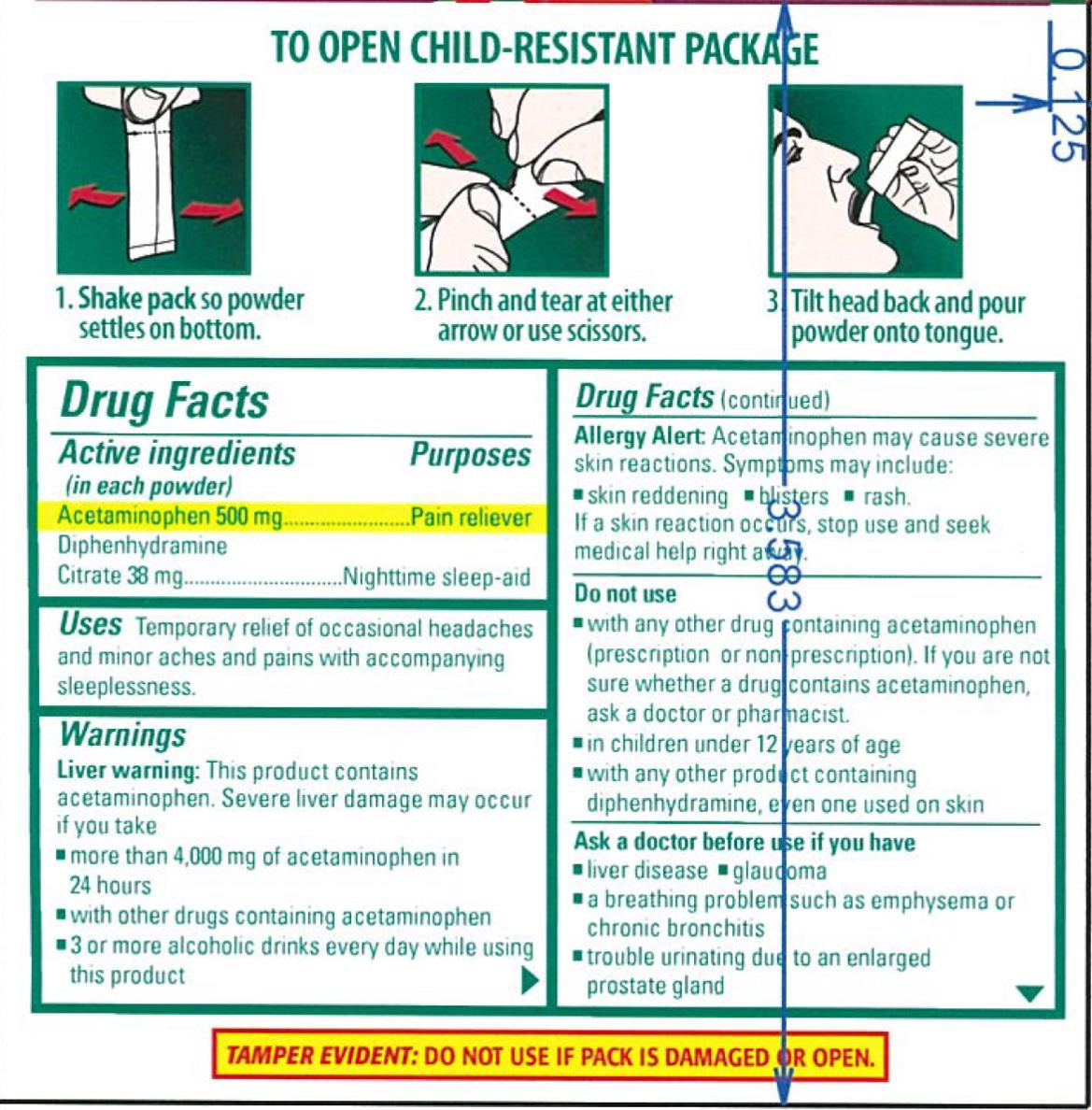 DRUG LABEL: GOODYS PM
NDC: 63029-656 | Form: POWDER
Manufacturer: Medtech Products Inc.
Category: otc | Type: HUMAN OTC DRUG LABEL
Date: 20241025

ACTIVE INGREDIENTS: ACETAMINOPHEN 500 mg/1 1; DIPHENHYDRAMINE CITRATE 38 mg/1 1
INACTIVE INGREDIENTS: CITRIC ACID MONOHYDRATE; DOCUSATE SODIUM; FUMARIC ACID; LACTOSE MONOHYDRATE; MAGNESIUM STEARATE; POTASSIUM CHLORIDE; SILICON DIOXIDE; SODIUM BENZOATE; TRISODIUM CITRATE DIHYDRATE; GLYCINE

Goodys PM - 63029-656

Drug Facts

Active ingredients

(in each powder)
Acetaminophen 500 mg
Diphenhydramine Citrate 38 mg

Purposes

Pain reliever
Nighttime sleep-aid

Uses

• temporary relief of occasional headaches and minor aches and pains with accompanying sleeplessness

Warnings

Liver warning: This product contains acetaminophen. Severe liver damage may occur if you take

• more than 4,000 mg of acetaminophen in 24 hours
• with other drugs containing acetaminophen
• 3 or more alcoholic drinks every day while using this product

Allergy Alert: Acetaminophen may cause severe skin reactions. Symptoms may include:

● skin reddening ● blisters ● rash. If a skin reaction occurs, stop use and seek medical help right away.

Do not use

• with any other drug containing acetaminophen (prescription or nonprescription). If you are not sure whether a drug contains acetaminophen, ask a doctor or pharmacist.
• in children under 12 years of age
• with any other product containing diphenhydramine, even one used on skin

Ask a doctor before use if you have

• liver disease
• glaucoma
• a breathing problem such as emphysema or chronic bronchitis
• trouble urinating due to an enlarged prostate gland

Ask a doctor or pharmacist before use if you are taking

• the blood thinning drug warfarin
• sedatives or tranquilizers

When using this product

• drowsiness will occur
• avoid alcoholic drinks
• be careful when driving a motor vehicle or operating machinery

Stop use and ask a doctor if

• sleeplessness persists continuously for more than 2 weeks. Insomnia may be a symptom of a serious underlying medical illness.
• pain gets worse or lasts more than 10 days
• redness or swelling is present
• any new symptoms appear
These could be signs of a serious condition.

If pregnant or breast-feeding,

ask a health professional before use.

Overdose warning:

Taking more than the recommended dose can cause serious health problems. In case of overdose, get medical help or contact Poison Control Center (1-800-222-1222) right away. Quick medical attention is critical for adults as well as for children even if you do not notice any signs or symptoms.

Directions

• do not take more than directed (see overdose warning)
• adults and children 12 years of age and over: take 2 powders at bedtime, if needed, or as directed by a doctor. Drink a full glass of water with each dose, or may stir powder into a glass of water or other liquid.
• do not give to children under 12 years of age

Other Information

• each powder contains: potassium 42 mg
• store below 25°C (77°F)

Inactive ingredients

citric acid, docusate sodium, fumaric acid, glycine, lactose monohydrate, magnesium stearate, potassium chloride, silica gel, sodium benzoate, sodium citrate dihydrate

Questions or comments?

1-866-255-5197

Principal Display Panel

Goody’s PM
Acetaminophen • Diphenhydramine Citrate
Pain Reliever/ Nighttime sleep-aid
FOR PAIN WITH SLEEPLESSNESS
16 Powder Packs